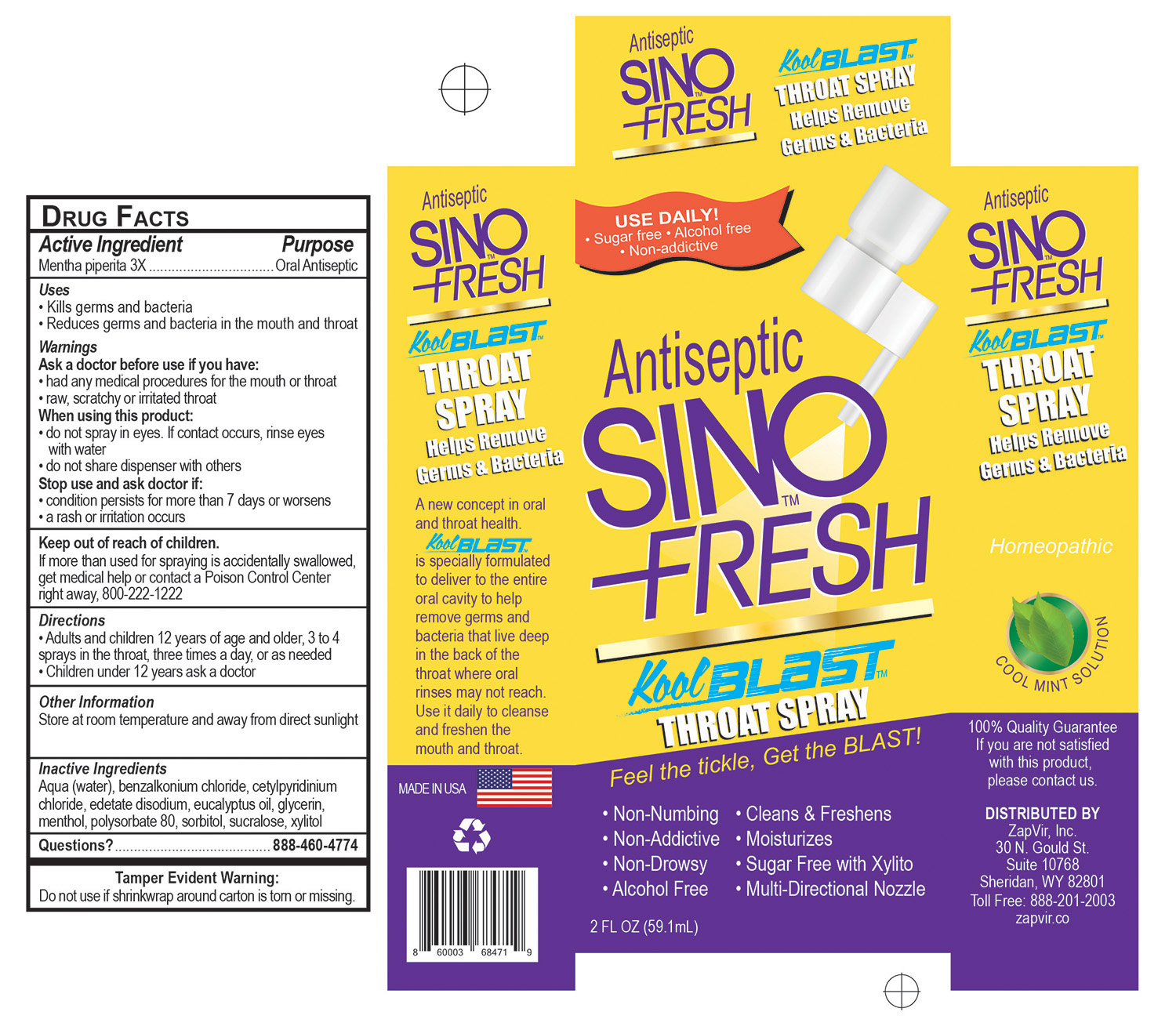 DRUG LABEL: SinoFresh KoolBlast
NDC: 79961-003 | Form: SPRAY
Manufacturer: ZapVir Inc.
Category: homeopathic | Type: HUMAN OTC DRUG LABEL
Date: 20201012

ACTIVE INGREDIENTS: MENTHA PIPERITA 0.1 g/100 g
INACTIVE INGREDIENTS: SORBITOL; EDETATE DISODIUM; EUCALYPTUS OIL; MENTHOL; SUCRALOSE; GLYCERIN; POLYSORBATE 80; BENZALKONIUM CHLORIDE; CETYLPYRIDINIUM CHLORIDE; WATER; XYLITOL

SinoFresh KoolBlast Oral Antiseptic Spray

Active Ingredients

Mentha Piperita 3X

Purpose

Oral Antiseptic

Uses
• Kills germs and bacteria
• Reduces germs and bacteria in the mouth and throat

Warnings

Ask a doctor before use if you have:
• had any medical procedures for the mouth or throat
• raw, scratchy or irritated throat
When using this product:
• do not spray in eyes. If contact occurs, rinse eyes
with water
• do not share dispenser with others

Stop Use

Stop use and ask doctor if:
• condition persists for more than 7 days or worsens
• a rash or irritation occurs

Keep Our of Reach of Children

Keep out of reach of children.
If more than used for spraying is accidentally swallowed,
get medical help or contact a Poison Control Center
right away, 800-222-1222

Dosage and Administration

Directions
• Adults and children 12 years of age and older, 3 to 4
sprays in the throat, three times a day, or as needed
• Children under 12 years ask a doctor

Indications and Usage

Oral Antiseptic

• Reduces germs and bacteria in the mouth and throat

Inactive Ingredients

Inactive Ingredients: Aqua (water), benzalkonium chloride, cetylpyridinium chloride, edetate disodium, eucalyptus oil, glycerin,
menthol, polysorbate 80, sorbitol, sucralose, xylitol

Warnings

Ask a doctor before use if you have:
• had any medical procedures for the mouth or throat
• raw, scratchy or irritated throat
When using this product:
• do not spray in eyes. If contact occurs, rinse eyes
with water
• do not share dispenser with others
Stop use and ask doctor if:
• condition persists for more than 7 days or worsens
• a rash or irritation occurs